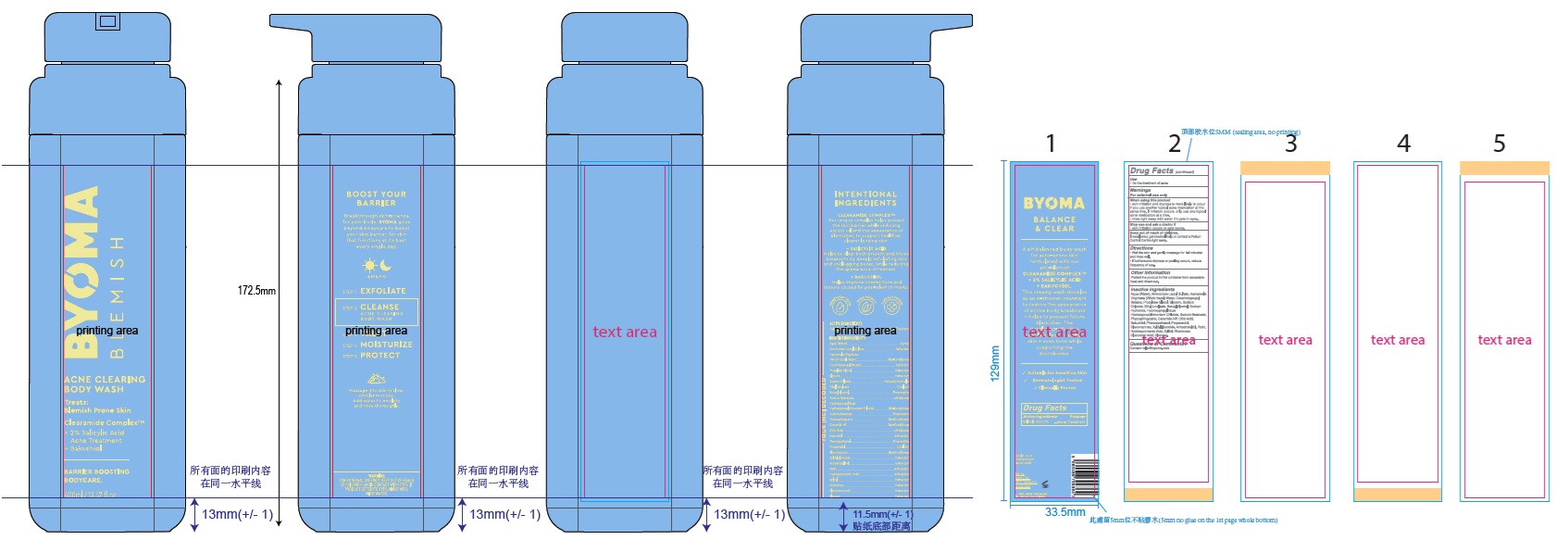 DRUG LABEL: Byoma Acne Clearing Body Wash
NDC: 84821-005 | Form: LIQUID
Manufacturer: Byoma Ltd
Category: otc | Type: HUMAN OTC DRUG LABEL
Date: 20250423

ACTIVE INGREDIENTS: SALICYLIC ACID 20 mg/1 mL
INACTIVE INGREDIENTS: SODIUM BENZOATE; PROPYLENE GLYCOL; GLUCOSE; WATER; BAKUCHIOL; HAMAMELIS VIRGINIANA TOP WATER; PHYTOSPHINGOSINE; COCAMIDOPROPYL BETAINE; SODIUM HYDROXIDE; RHAMNOSE; ETHYL LINOLEATE; HYDROXYPROPYL GUAR HYDROXYPROPYLTRIMONIUM CHLORIDE; CITRIC ACID MONOHYDRATE; AMMONIUM LAURYL SULFATE; GLYCERIN; BENZYL ALCOHOL; PHENOXYETHANOL; ANHYDROXYLITOL; HYDROXYCINNAMIC ACID; XYLITOL; GLUCURONIC ACID; RUTIN; SODIUM CHLORIDE; PROPANEDIOL; CERAMIDE NP; GLUCOMANNAN; XYLITYLGLUCOSIDE

Byoma Acne Clearing Body Wash

Active ingredient

Salicylic Acid 2%

Purpose

Acne Treatment

Use

- for the treatment of acne

Warnings

For external use only

When using this product

- skin irritation and dryness is more likely to occur if you use another topical acne medication at the same time. If irritation occurs, only use one topical acne medication at a time.
- rinse right away with water if it gets in eyes.

Stop use and ask a doctor if

- skin irritation occurs or gets worse.

Keep out of reach of children.

If swallowed, get medical help or contact a Poison Control Centre right away.

Directions

- Wet the skin and gently massage for 1-2 minutes and rinse well.
- If bothersome dryness or peeling occurs, reduce frequency of use.

Other Information

Protect the product in this container from excessive heat and direct sun.

Inactive Ingredients

Aqua (Water), Ammonium Lauryl Sulfate, Hamamelis Virginiana (Witch Hazel) Water, Cocamidopropyl Betaine, Propylene Glycol, Glycerin, Sodium Chloride, Ethyl Linoleate, Benzyl Alcohol, Sodium Hydroxide, Hydroxypropyl Guar Hydroxypropyltrimonium Chloride, Sodium Benzoate, Phytosphingosine, Ceramide NP, Citric Acid, Bakuchiol, Phenoxyethanol, Propanediol, Glucomannan, Xylitylglucoside, Anhydroxylitol, Rutin, Hydroxycinnamic Acid, Xylitol, Rhamnose, Glucuronic Acid, Glucose.

Questions or Comments?

Contact hello@byoma.com